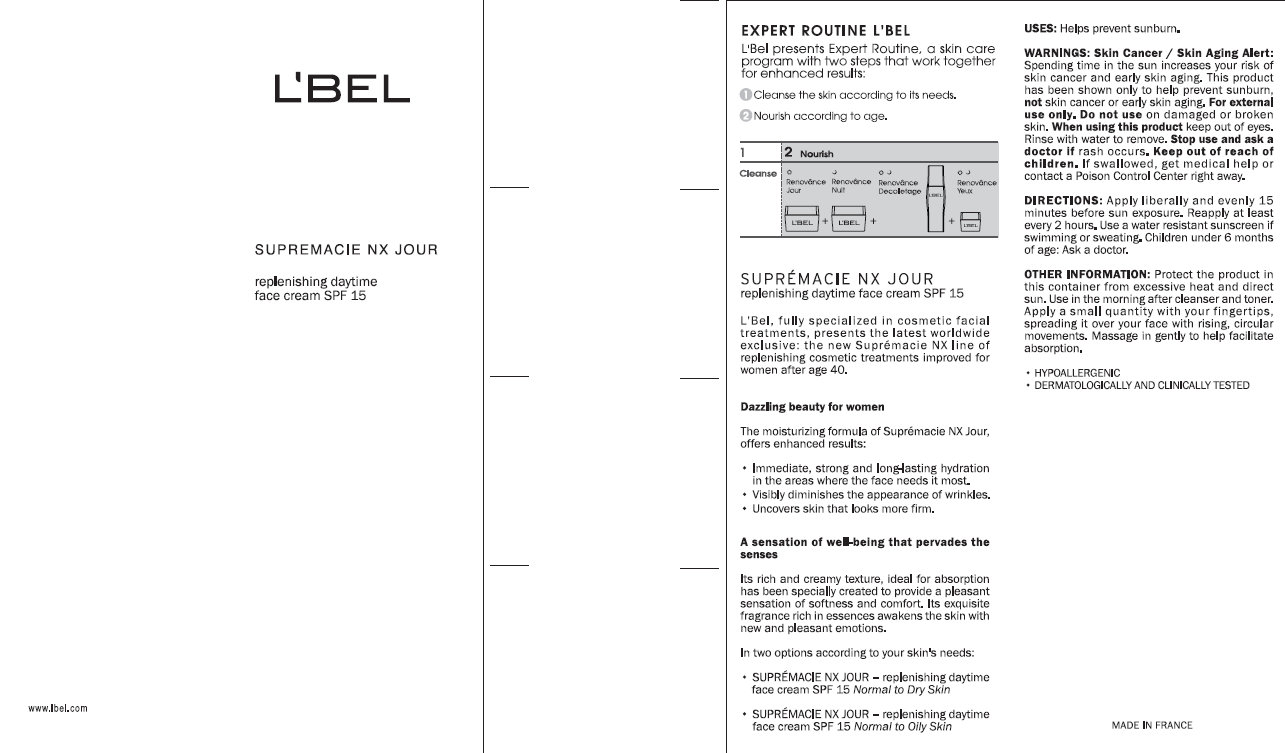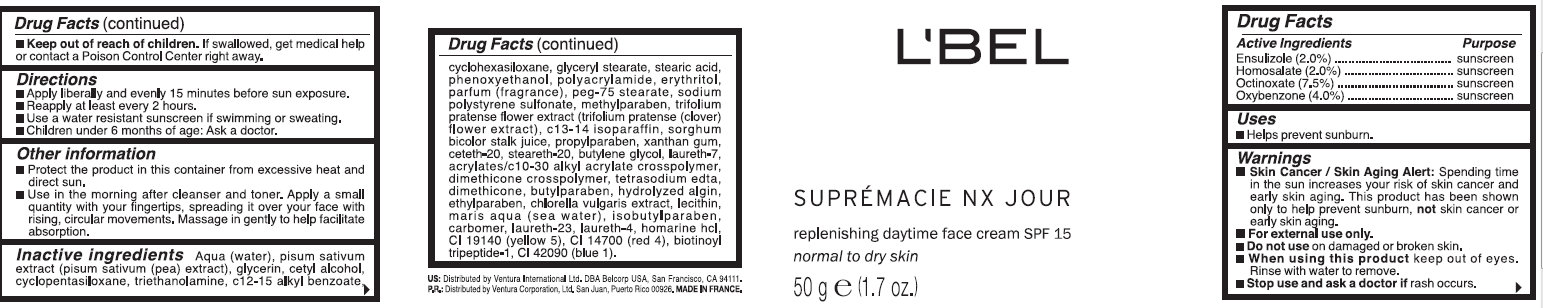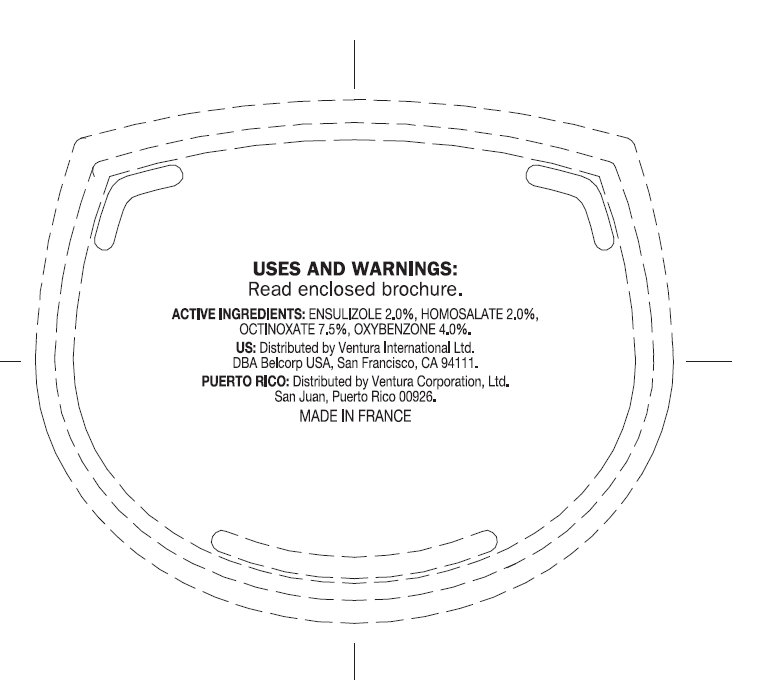 DRUG LABEL: LBEL SUPREMACIE NX JOUR Replenishing Treatment Daytime Face SPF 15 Normal To Dry Skin
NDC: 43455-0005 | Form: CREAM
Manufacturer: Ventura International, LTD
Category: otc | Type: HUMAN OTC DRUG LABEL
Date: 20120328

ACTIVE INGREDIENTS: ENSULIZOLE 2 g/100 g; HOMOSALATE 2 g/100 g; OCTINOXATE 7.5 g/100 g; OXYBENZONE 4 g/100 g
INACTIVE INGREDIENTS: WATER; PEA; GLYCERIN; CETYL ALCOHOL; CYCLOMETHICONE 5; TROLAMINE; ALKYL (C12-15) BENZOATE; CYCLOMETHICONE 6; GLYCERYL MONOSTEARATE; STEARIC ACID; PHENOXYETHANOL; ERYTHRITOL; PEG-75 STEARATE; SODIUM POLYSTYRENE SULFONATE; METHYLPARABEN; TRIFOLIUM PRATENSE FLOWER; C13-14 ISOPARAFFIN; SORGHUM BICOLOR STEM JUICE; PROPYLPARABEN; XANTHAN GUM; CETETH-20; STEARETH-20; BUTYLENE GLYCOL; LAURETH-7; CARBOMER INTERPOLYMER TYPE A (55000 MPA.S); EDETATE SODIUM; DIMETHICONE; BUTYLPARABEN; METHYLPARABEN; CHLORELLA VULGARIS; ISOBUTYLPARABEN; LAURETH-23; LAURETH-4; FD&C YELLOW NO. 5; FD&C RED NO. 4; BIOTINOYL TRIPEPTIDE-1; FD&C BLUE NO. 1

L'BEL SUPREMACIE NX JOUR Replenishing Treatment Daytime Face Cream SPF 15 Normal To Dry Skin

Active Ingredients

ENSULIZOLE (2.0%)
HOMOSALATE (2.0%)
OCTINOXATE (7.5%)
OXYBENZONE (4.0%)

Uses

- Helps prevent sunburn.

Warnings

- Skin Cancer / Skin Aging Alert: Spending time in the sun increases your risk of skin cancer and early skin aging. This product has been shown only to help prevent sunburn, not skin cancer or early skin aging.
- For external use only.

When using this product

keep out of eyes. Rinse with water to remove.

Stop use and ask a doctor if

rash occurs.

Keep out of reach of children.

If swallowed, get medical help or contact a Poison Control Center right away.

Directions

- Apply liberally and evenly 15 minutes before sun exposure.
- Reapply at least every 2 years.
- Use a water resistant sunscreen if swimming or sweating.
- Children under 6 months of age: Ask a doctor.

Other Information

- Protect the product in this container from excessive heat and direct sun.
- Use in the morning after cleanser and toner. Apply a small quantity with your fingertips, spreading it over your face with rising, circular movements. Message in gently to help facilitate absorption.

Inactive Ingredients

Aqua (water), pisum sativum extract (pisum sativum (pea) extract), glycerin, cetyl alcohol, cyclopentasiloxane, triethanolamine, c12-15 alkyl benzoate, cyclohexasiloxane, glyceryl stearate, stearic acid, phenoxyethanol,polyacrylamide, erythritol,parfum (fragrance), peg-75 stearate, sodium polystyrene sulfonate,methylparaben, trifolium pratense flower extract(trifolium pratense (clover) flower extract), c13-14 isoparaffin,sorghum bicolor stalk juice, propylparaben, xanthan gum, ceteth-20,steareth-20, butylene glycol, laureth-7, acrylates/c10-30 alkyl acrylate crosspolymer, tetrasodium edta, dimethicone, butylparaben, hydrolyzed algin, ethylparaben, chlorella vulgaris extract, lecithin, maris aqua (sea water), isobutylparaben, carbomer, laureth-23, laureth-4, homarine hcl, ci 19140 (yellow 5),ci 14700 (red 4), biotinoyl tripeptide-1, ci 42090 (blue 1).

Purpose

Sunscreen

EXPERT ROUTINE L'BEL

L'Bel presents Expert Routine, a skin care program with two steps that work together for enhanced results:
1. Cleanse the skin according to its needs
2. Nourish according to the age.
SUPREMACIE NX JOUR
replenishing daytime face cream SPF 15
L'Bel, fully specialized in cosmetic facial treatment, presents the latest worldwide exclusive: the new Supremacie NX line of replenishing cosmetic treatments improved for women after age 40.
Dazzling beauty for women
The moisturizing formula of Supremacie NX Jour, Offers enhanced results:

- Immediate, strong and long-lasting hydration in the areas where the face needs it most.
- Visibly diminishes the appearance of wrinkles.
- Uncovers skin that looks more firm.

A sensation of well-being that pervades the senses
Its rich and creamy texture, ideal for absorption has been specially created to provide a pleasant sensation of softness and comfort. Its exquisite fragrance rich in essences awakens the skin with new and pleasant emotions.
In two options according to your skin's needs:

- SUPREMACIE NX JOUR - replenishing daytime face cream SPF 15 Normal to Dry Skin

- SUPREMACIE NX JOUR - replenishing daytime face cream SPF 15 Normal to Oily Skin

USES: Helps prevent sunburn.
WARNINGS: Skin Cancer / Skin Aging Alert: Spending time in the sun increases your risk of skin cancer and early skin aging. This product has been shown only to help prevent sunburn, not skin cancer or early skin aging. For external use only. Do not use on damaged or broken skin. When using this product keep out of eyes. Rinse with water to remove. Stop use and ask a doctor if rash occurs. Keep out of reach of children. If swallowed, get medical help or contact a Poison Control Center right away.
Directions: Apply liberally and evenly 15 minutes before sun exposure. Reapply at least every 2 hours.Use a water resistant sunscreen if swimming or sweating. Children under 6 months of age: Ask a doctor.
Other information: Protect the product in this container from excessive heat and direct sun. Use in the morning after cleanser and toner. Apply a small quantity with your fingertips, spreading it over your face with rising, circular movements. Message in gently to help facilitate absorption.

- HYPOALLERGENIC
- DERMATOLOGICALLY AND CLINICALLY TESTED

PACKAGE LABEL

L'BEL
SUPREMACIE NX JOUR
replenishing daytime face cream SPF 15
normal to dry skin
50 g e (1.7 oz..)
US: Dist. by Ventura International Ltd. DBA Belcorp USA, San Francisco, CA 94111.
P.R.: Dist. by Ventura Corporation Ltd. San Juan, Puerto Rico 00926 MADE IN FRANCE.